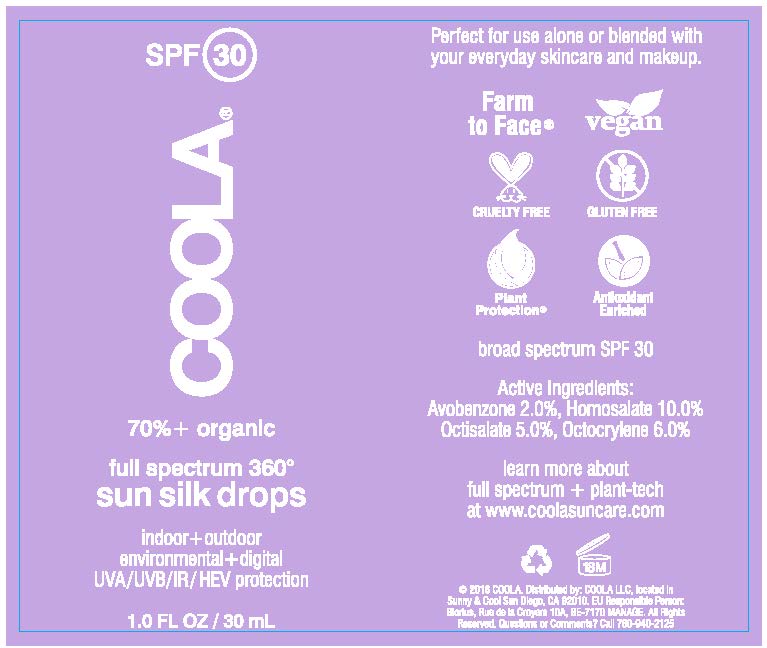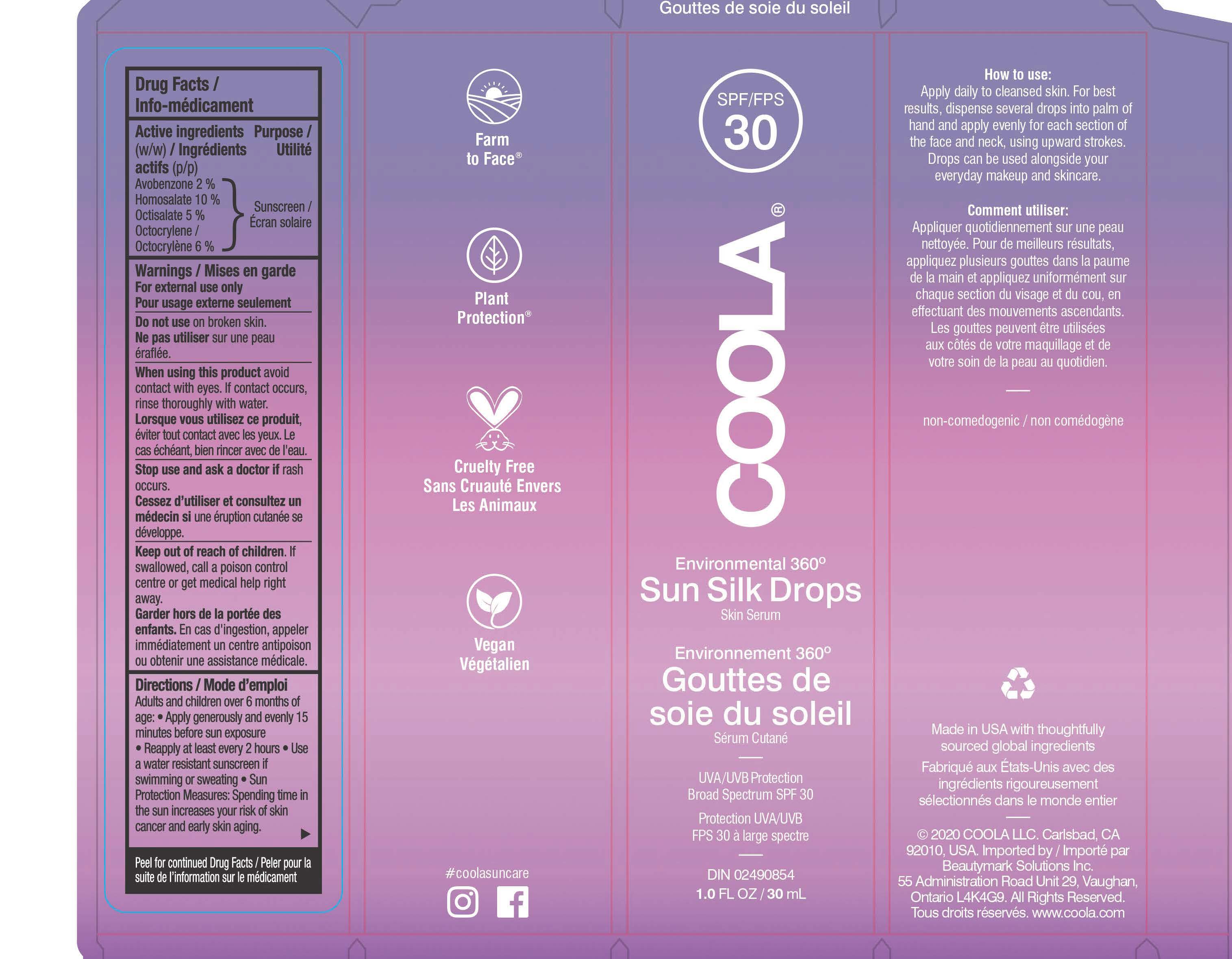 DRUG LABEL: COOLA Full Spectrum 360 Sun Silk Drops
NDC: 21839-620 | Form: LIQUID
Manufacturer: Gordon Laboratories, Inc.
Category: otc | Type: HUMAN OTC DRUG LABEL
Date: 20191218

ACTIVE INGREDIENTS: AVOBENZONE 20 mg/1 mL; HOMOSALATE 100 mg/1 mL; OCTISALATE 50 mg/1 mL; OCTOCRYLENE 60 mg/1 mL
INACTIVE INGREDIENTS: WATER; ALPHA-TOCOPHEROL ACETATE; SODIUM STEAROYL GLUTAMATE; HYALURONATE SODIUM; SODIUM BENZOATE; PROPANEDIOL; OLIVE OIL; GLUCONOLACTONE; ALOE VERA LEAF; COCOA; SCHINUS MOLLE FRUITING TOP; JASMINUM SAMBAC FLOWER; GLYCERYL STEARATE SE; CITRUS AURANTIUM FLOWER OIL; SAFFLOWER OIL; NYLON-12; BUTYLOCTYL SALICYLATE; CHAMAEMELUM NOBILE FLOWER OIL; XANTHAN GUM; JOJOBA OIL; GLYCERIN; DICAPRYLYL CARBONATE; MEDIUM-CHAIN TRIGLYCERIDES; BUTYLENE GLYCOL

COOLA Full Spectrum 360 Sun Silk Drops SPF 30

DRUG FACTS

Active ingredients

Avobenzone 2.0%, Homosalate 10.0%

Octisalate 5.0%, Octocrylene 6.0%

Purpose

Sunscreen

Uses
* helps prevent sunburn
* if used as directed with other sun protection measures (see Directions), decreases the rise of skin cancer and early skin aging caused by the sun

Warnings
For external use only
Do not use on damaged or broken skin
When using this product keep out of eyes. Rinse with water to remove.
Stop use and ask doctor if skin rash occurs
Keep out of reach of children. If prodcut is swallowed, get medical help or contact Poison Control Center right away.

Do not use on damaged or broken skin

When using this product keep out of eyes. Rinse with water to remove

Stop use and ask doctor if skin rash occurs

Keep out of reach of children. If product is swallowed, get medical help or contact a Poison Control Center right away.

Directions
* shake well * apply liberally 15 minutes before sun exposure
* reapply: * after swimming or sweating * immediately after towel drying * at least every 2 hours
* Sun Protection Measures. Spending time in the sun increases your risk of skin cancer and early aging. To decrease this risk, regularly use a sunscreen with a broad spectrum SPF of 15 or higher and other sun protection measures including: * limit time in the sun, especially from: 10 a.m. – 2 p.m.
* wear long-sleeve shirts, pants, hats, and sunglasses
* children under 6 months: Ask a doctor

INACTIVE INGREDIENT

Aloe Barbadensis Leaf Extract (Organic), Anthemis Nobilis (Chamomile) Flower Oil, Butylene Glycol, Butyloctyl Salicylate, Calcium Gluconate, Caprylic/Capric Triglyceride, Carthamus Tinctorius (Organic Safflower) Seed Oil, Citrus Aurantium Amara (Bitter Orange) Flower Extract, Citrus Aurantium Amara (Bitter Orange) Leaf/Twig Extract, Dicaprylyl Carbonate, Glycerin (Organic), Glyceryl Stearate Se, Jasminum Sambac (Jasmine) Leaf Cell Extract, Nylon-12, Olea Europaea (Organic Olive) Fruit Oil, Plankton Leaf Extract, Propanediol, Schinus Molle Extract, Simmondsia Chinensis (Organic Jojoba) Seed Oil, Sodium Benzoate, Sodium Hyaluronate, Sodium Stearoyl Glutamate, Theobroma Cacao (Cocoa) Seed Extract, Tocopheryl Acetate, Water (Aqua), Xanthan Gum

Other information
* protect this product from excessive heat and direct sun

Questions or comments? Call 760-940-2125

How to use:

Apply daily to cleansed skin. For best

results, dispense several drops as needed

into palm of hand and apply evenly across

face and neck using upward strokes. Drops

are perfect for use alone or blended with

your everyday skincare and makeup.